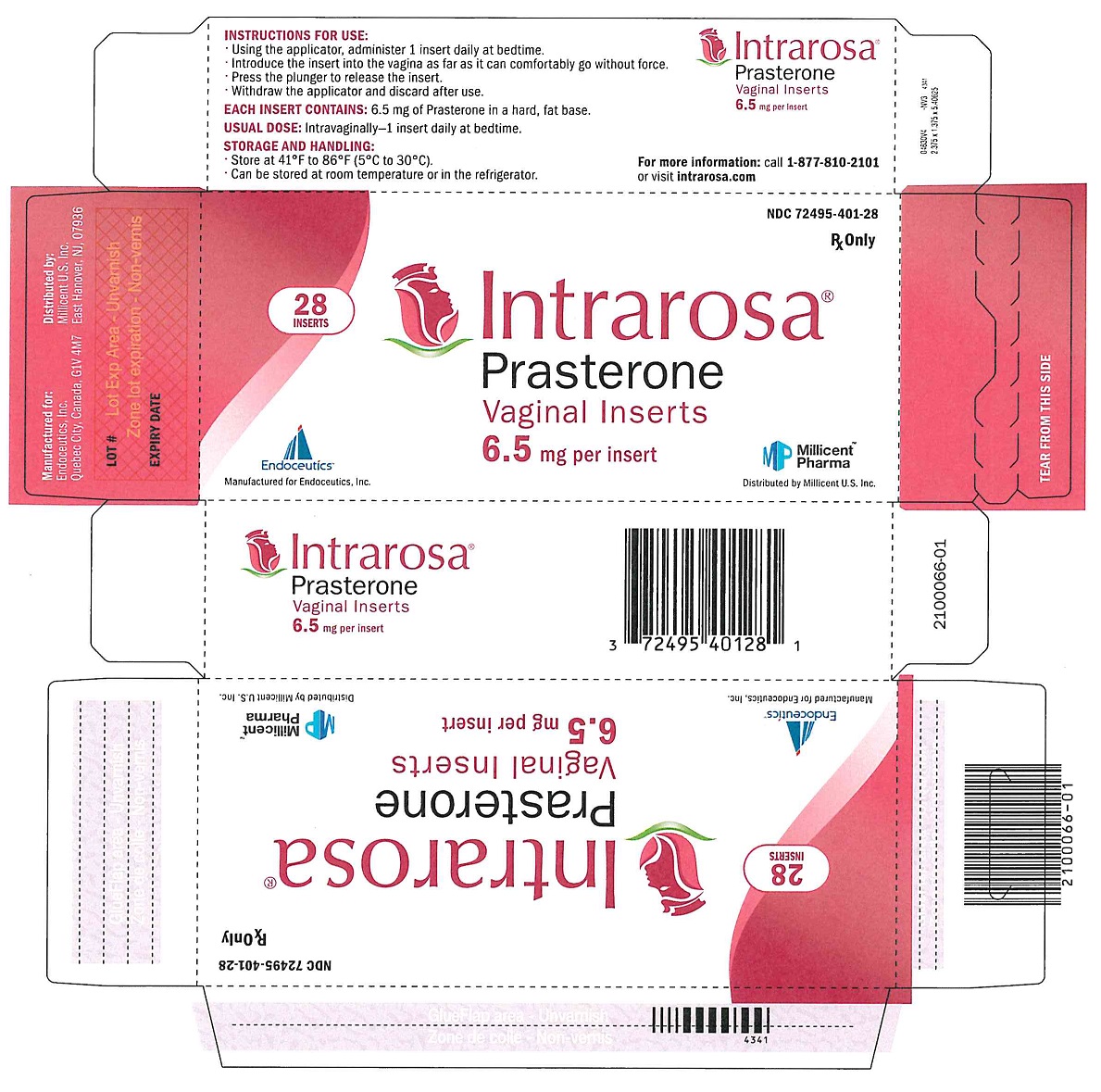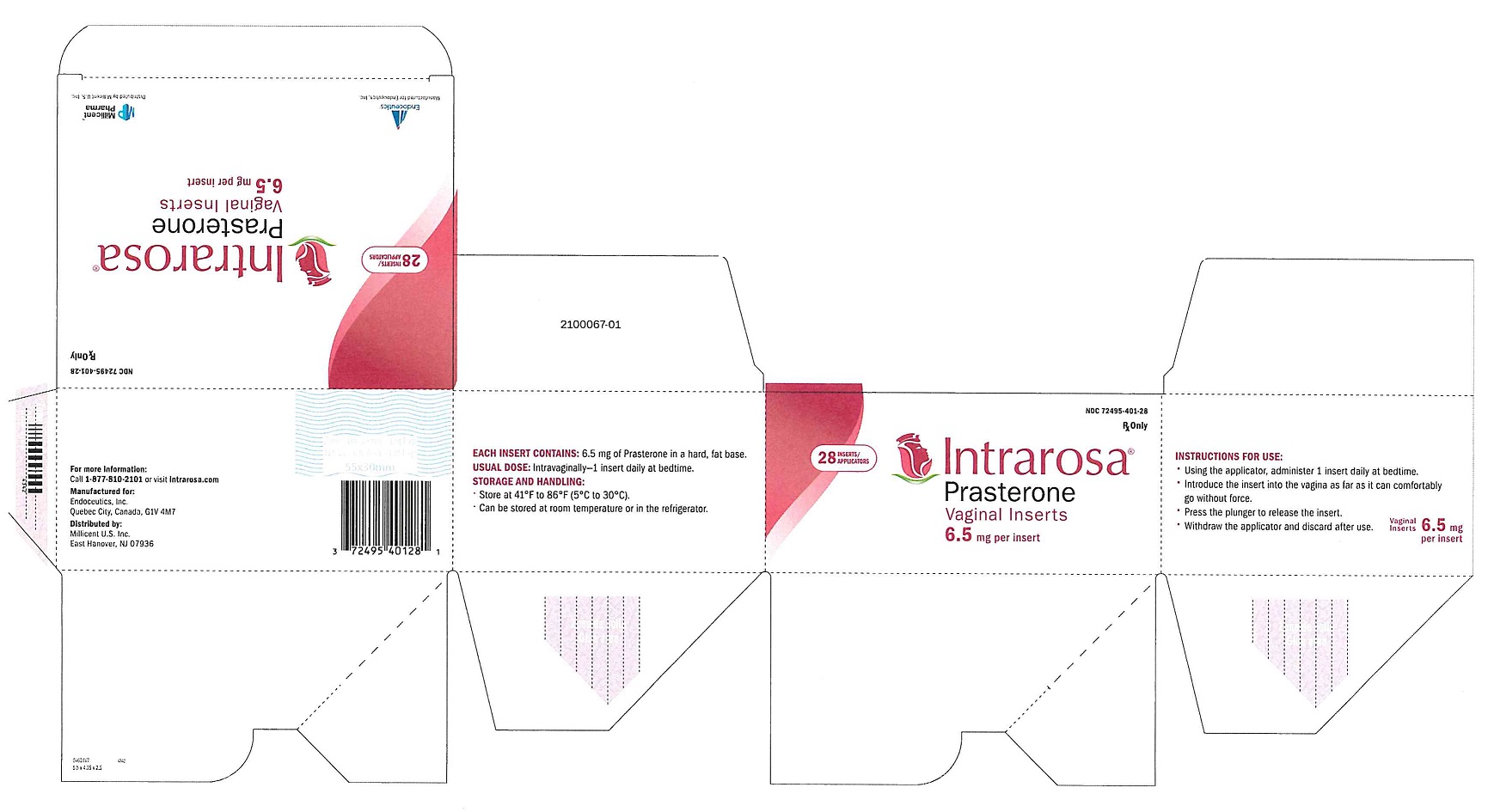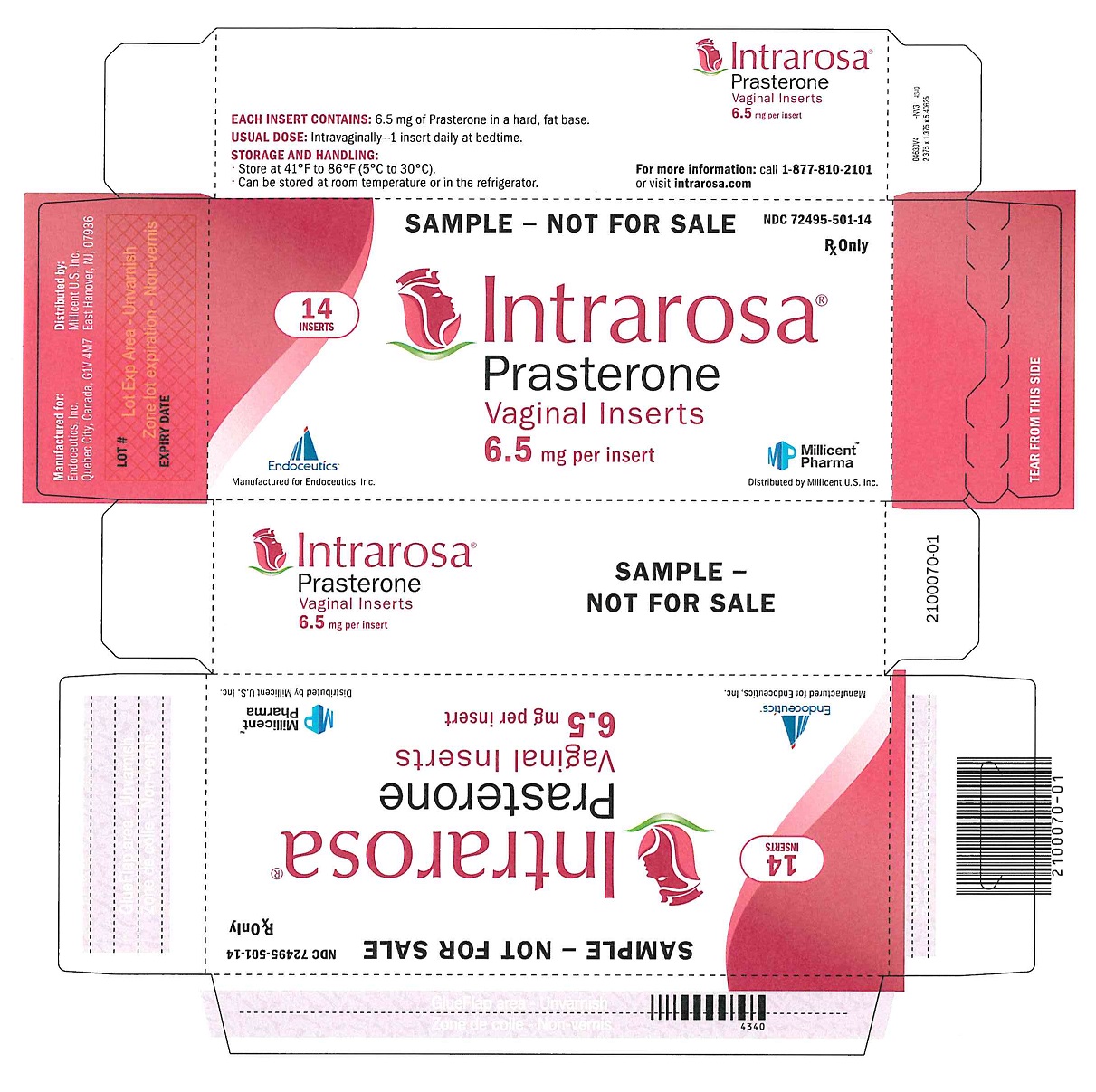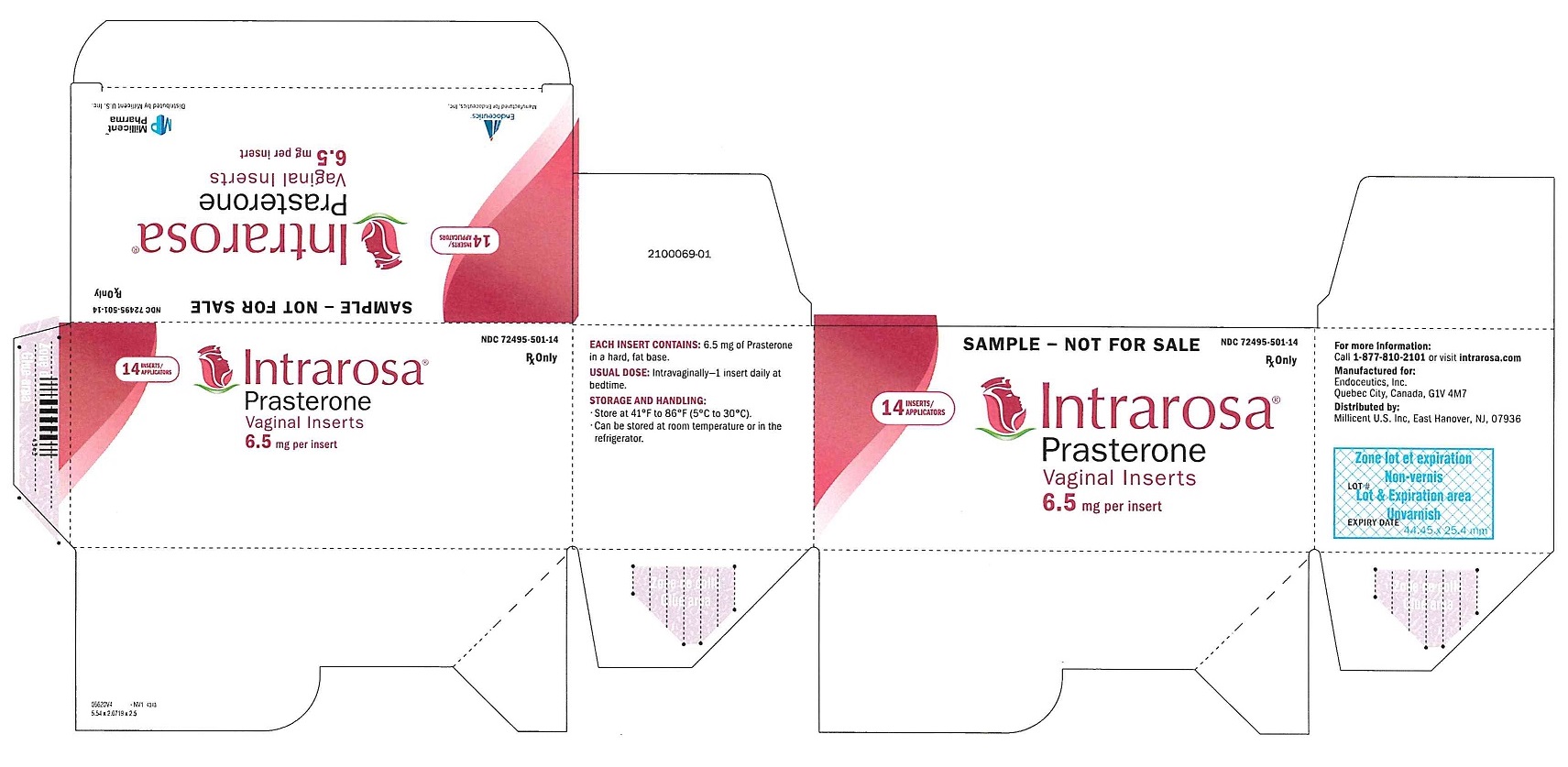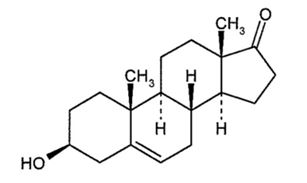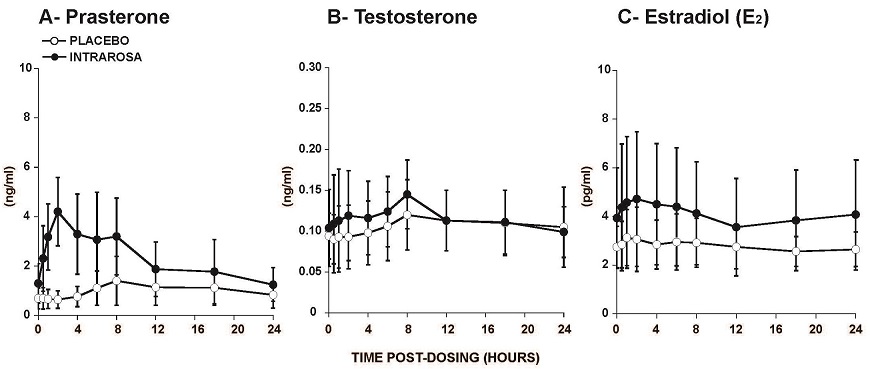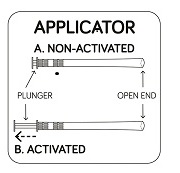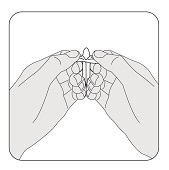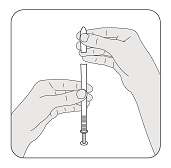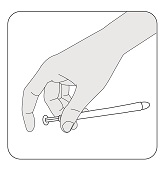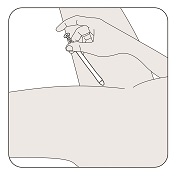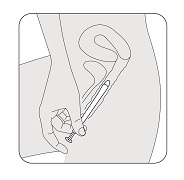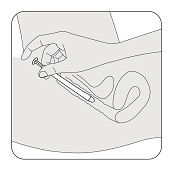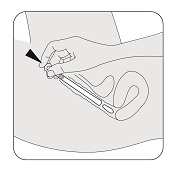 DRUG LABEL: Intrarosa
NDC: 72495-501 | Form: INSERT
Manufacturer: Millicent US, Inc.
Category: prescription | Type: HUMAN PRESCRIPTION DRUG LABEL
Date: 20250101

ACTIVE INGREDIENTS: PRASTERONE 6.5 mg/1 1
INACTIVE INGREDIENTS: HYDROGENATED COCO-GLYCERIDES

HIGHLIGHTS OF PRESCRIBING INFORMATION

These highlights do not include all the information needed to use INTRAROSA® safely and effectively. See full prescribing information for INTRAROSA®.
INTRAROSA® (prasterone) vaginal inserts
Initial U.S. Approval: 2016

1 INDICATIONS AND USAGE

INTRAROSA® is a steroid indicated for the treatment of moderate to severe dyspareunia, a symptom of vulvar and vaginal atrophy, due to menopause. (1)

2 DOSAGE AND ADMINISTRATION

One vaginal insert, once daily at bedtime. (2)

3 DOSAGE FORMS AND STRENGTHS

Vaginal Insert: 6.5 mg of prasterone. (3)

4 CONTRAINDICATIONS

Undiagnosed abnormal genital bleeding. (4)

5 WARNINGS AND PRECAUTIONS

Current or Past History of Breast Cancer. (5.1)

6 ADVERSE REACTIONS

In four 12-week randomized, placebo-controlled clinical trials, the most common adverse reaction with an incidence ≥ 2 percent was vaginal discharge. (6.1)

In one 52-week open-label clinical trial, the most common adverse reactions with an incidence ≥ 2 percent were vaginal discharge and abnormal Pap smear. (6.1)

To report SUSPECTED ADVERSE REACTIONS, contact Millicent U.S. Inc at 1-877-810-2101 or FDA at 1-800-FDA-1088 or www.fda.gov/medwatch.

FULL PRESCRIBING INFORMATION

1 INDICATIONS AND USAGE

INTRAROSA® is a steroid indicated for the treatment of moderate to severe dyspareunia, a symptom of vulvar and vaginal atrophy, due to menopause.

2 DOSAGE AND ADMINISTRATION

Administer one INTRAROSA vaginal insert once daily at bedtime, using the provided applicator.

3 DOSAGE FORMS AND STRENGTHS

Vaginal insert: 6.5 mg of prasterone, smooth, white to off-white solid fat bullet-shaped, measuring 28 mm in length, 9 mm in width at its wider end, and weighing 1.2 gram.

4 CONTRAINDICATIONS

Undiagnosed abnormal genital bleeding: Any postmenopausal woman with undiagnosed, persistent or recurring genital bleeding should be evaluated to determine the cause of the bleeding before consideration of treatment with INTRAROSA.

5 WARNINGS AND PRECAUTIONS

5.1 Current or Past History of Breast Cancer

Estrogen is a metabolite of prasterone. Use of exogenous estrogen is contraindicated in women with a known or suspected history of breast cancer. INTRAROSA has not been studied in women with a history of breast cancer.

6 ADVERSE REACTIONS

6.1 Clinical Trials Experience

Because clinical trials are conducted under widely varying conditions, adverse reaction rates observed in the clinical trials of a drug cannot be directly compared to rates in the clinical trials of another drug and may not reflect the rates observed in practice.

In four (4) placebo-controlled, 12-week clinical trials [91% - White Caucasian non-Hispanic women, 7% - Black or African American women, and 2% - "Other" women, average age 58.8 years of age (range 40 to 80 years of age)], vaginal discharge is the most frequently reported treatment-emergent adverse reaction in the INTRAROSA treatment group with an incidence of ≥ 2 percent and greater than reported in the placebo treatment group. There were 38 cases in 665 participating postmenopausal women (5.71 percent) in the INTRAROSA treatment group compared to 17 cases in 464 participating postmenopausal women (3.66 percent) in the placebo treatment group.

In a 52-week non-comparative clinical trial [92% - White Caucasian non-Hispanic women, 6% - Black or African American women, and 2% - "Other" women, average age 57.9 years of age (range 43 to 75 years of age)], vaginal discharge and abnormal Pap smear at 52 weeks were the most frequently reported treatment-emergent adverse reaction in women receiving INTRAROSA with an incidence of ≥ 2 percent. There were 74 cases of vaginal discharge (14.2 percent) and 11 cases of abnormal Pap smear (2.1 percent) in 521 participating postmenopausal women. The eleven (11) cases of abnormal Pap smear at 52 weeks include one (1) case of low-grade squamous intraepithelial lesion (LSIL), and ten (10) cases of atypical cells of undetermined significance (ASCUS).

8 USE IN SPECIFIC POPULATIONS

8.1 Pregnancy

Risk Summary

INTRAROSA is indicated only in postmenopausal women. There are no data with INTRAROSA use in pregnant women regarding any drug-associated risks. Animal reproduction studies have not been conducted with prasterone.

8.2 Lactation

Risk Summary

INTRAROSA is indicated only in postmenopausal women. There is no information on the presence of prasterone in human milk, the effects on the breastfed infant, or the effects on milk production.

8.4 Pediatric Use

Safety and effectiveness have not been established in pediatric patients.

8.5 Geriatric Use

Of the 1522 prasterone-treated postmenopausal women enrolled in the four placebo-controlled 12-week and one open-label 52-week clinical trial, 19 and 11 percent, respectively, were 65 years of age or older.

8.6 Renal Impairment

The effect of renal impairment on the pharmacokinetics of prasterone has not been studied.

8.7 Hepatic Impairment

The effect of hepatic impairment on the pharmacokinetics of prasterone has not been studied.

11 DESCRIPTION

INTRAROSA (prasterone) vaginal insert is a vaginally administered steroid. Prasterone is identified chemically as 3β-hydroxyandrost-5-en-17-one. It has the empirical formula C19H28O2 with a molecular weight of 288.424 g/mol. Prasterone is a white to off-white crystalline powder insoluble in water and soluble in sodium lauryl sulfate (SLS). The structural formula is:

Each INTRAROSA (prasterone) vaginal insert contains 6.5 mg of prasterone in 1.3 ml of off-white hard fat (Witepsol).

12 CLINICAL PHARMACOLOGY

12.1 Mechanism of Action

Prasterone is an inactive endogenous steroid and is converted into active androgens and/or estrogens. The mechanism of action of INTRAROSA in postmenopausal women with vulvar and vaginal atrophy is not fully established.

12.3 Pharmacokinetics

In a study conducted in postmenopausal women, administration of the INTRAROSA vaginal insert once daily for 7 days resulted in a mean prasterone Cmax and area under the curve from 0 to 24 hours (AUC0-24) at Day 7 of 4.4 ng/mL and 56.2 ng·h/mL, respectively, which were significantly higher than those in the group treated with placebo (Table 1). The Cmax and AUC0-24 of the metabolites testosterone and estradiol were also slightly higher in women treated with the INTRAROSA vaginal insert compared to those receiving placebo.

Table 1. Cmax and AUC0-24 of Prasterone, Testosterone, and Estradiol on Day 7 Following Daily Administration of Placebo or INTRAROSA (mean ± SD).
 |  | Placebo (N=9) | INTRAROSA (N=10)
Prasterone | Cmax (ng/mL) | 1.60 (±0.95) | 4.42 (±1.49)
Prasterone | AUC0-24 (ng·h/mL) | 24.82 (±14.31) | 56.17 (±28.27)
Testosterone | Cmax (ng/mL) | 0.12 (±0.04)^1 | 0.15 (±0.05)
Testosterone | AUC0-24 (ng·h/mL) | 2.58 (±0.94)^1 | 2.79 (±0.94)
Estradiol | Cmax (pg/mL) | 3.33 (±1.31) | 5.04 (±2.68)
Estradiol | AUC0-24 (pg·h/mL) | 66.49 (±20.70) | 96.93 (±52.06)
1: N=8

Figure 1. Serum Concentrations of Prasterone (A), Testosterone (B), and Estradiol (C) Measured Over a 24h Period on Day 7 Following Daily Administration of Placebo or INTRAROSA (mean ± SD).

In two primary efficacy trials, daily administration of INTRAROSA vaginal insert for 12 weeks increased mean serum Ctrough of prasterone and its metabolites testosterone and estradiol by 47%, 21% and 19% from baseline, respectively. This comparison based on Ctrough may underestimate the magnitude of increase in prasterone and metabolites’ exposure because it does not take into account the overall concentration-time profile following administration of INTRAROSA.

Metabolism

Exogenous prasterone is metabolized in the same manner as endogenous prasterone. Human steroidogenic enzymes such as hydroxysteroid dehydrogenases, 5α-reductases and aromatases transform prasterone into androgens and estrogens.

13 NONCLINICAL TOXICOLOGY

13.1 Carcinogenesis, Mutagenesis, Impairment of Fertility

Carcinogenesis

Long-term studies in animals to evaluate carcinogenic potential have not been conducted with prasterone. Two metabolites of prasterone, testosterone and estradiol, are carcinogenic in animals.

Mutagenesis

Prasterone was not genotoxic in the in vitro bacterial mutagenesis assay (Ames test), the in vitro chromosomal aberrations assay with human peripheral blood lymphocytes, and in vivo in the mouse bone marrow micronucleus assay.

Fertility

Fertility studies were not conducted with prasterone.

14 CLINICAL STUDIES

The effectiveness of INTRAROSA on moderate to severe dyspareunia, a symptom of vulvar and vaginal atrophy, due to menopause was examined in two primary 12-week placebo-controlled efficacy trials.

The first clinical trial (Trial 1) was a 12-week randomized, double-blind and placebo-controlled trial that enrolled 255 generally healthy postmenopausal women between 40 to 75 years of age (mean 58.6 years) who, at baseline, identified moderate to severe dyspareunia as their most bothersome symptom of vulvar and vaginal atrophy. In addition to moderate to severe dyspareunia, women had ≤ 5% superficial cells on vaginal smear and a vaginal pH > 5. Women were randomized in a 1:1:1 ratio between three treatment groups who received daily INTRAROSA (n=87), one active comparator vaginal insert (n=87), or placebo (n=81). All women were assessed for improvement from Baseline to Week 12 for four co-primary efficacy endpoints: most bothersome moderate to severe symptom of dyspareunia, the percentage of vaginal superficial cells, the percentage of parabasal cells, and vaginal pH.

The second clinical trial (Trial 2) was a 12-week randomized, double-blind and placebo-controlled trial that enrolled 558 generally healthy postmenopausal women between 40 to 80 years of age (mean 59.5 years) who, at baseline, had identified moderate to severe dyspareunia as their most bothersome symptom of vulvar and vaginal atrophy. In addition to dyspareunia, women had ≤ 5% superficial cells on vaginal smear and a vaginal pH > 5. Women were randomized in a 2:1 ratio to receive once daily vaginal insert containing 6.5 mg INTRAROSA (n=376) or placebo (n=182). The primary endpoints and study conduct were the same or similar to those in Trial 1.

The primary efficacy results obtained in the Intent-to-Treat (ITT) population in Trial 1 are shown in Table 2.

Table 2: Efficacy Summary in Primary 12-Week Trial 1: ITT Population (LOCF)

 | Placebo; N = 77 | INTRAROSA; N = 81
Dyspareunia; Baseline Mean Severity; Week 12 Mean Severity; Mean Change in Severity (SD); Difference from Placebo^1; p-value^2 | 2.58; 1.71; -0.87 (0.95); -; - | 2.63; 1.36; -1.27 (0.99); -0.40; 0.0132
% Superficial Cells; Baseline Mean; Week 12 Mean; Mean Change (SD); Difference from Placebo^1; p-value^2 | 0.73; 1.64; 0.91 (2.69); -; - | 0.68; 6.30; 5.62 (5.49); 4.71; <0.0001
% Parabasal Cells; Baseline Mean; Week 12 Mean; Mean Change (SD); Difference from Placebo^1; p-value^2 | 68.48; 66.86; -1.62 (28.22); -; - | 65.05; 17.65; -47.40 (42.50); -45.77; <0.0001
Vaginal pH; Baseline Mean; Week 12 Mean; Mean Change (SD); Difference from Placebo^1; p-value^2 | 6.51; 6.31; -0.21 (0.69); -; - | 6.47; 5.43; -1.04 (1.00); -0.83; <0.0001
^1Difference from placebo =INTRAROSA (Week 12 mean – Baseline mean) – Placebo (Week 12 mean – Baseline mean).
^2ANCOVA: Treatment as the main factor and Baseline value as the covariate.

The primary efficacy results obtained in the Intent-to-Treat (ITT) population in Trial 2 are shown in Table 3.

Table 3: Efficacy Summary in Primary 12-Week Trial 2: ITT Population (LOCF)

 | Placebo; N = 157 | INTRAROSA; N = 325
Dyspareunia; Baseline Mean Severity; Week 12 Mean Severity; Mean Change in Severity (SD); Difference from Placebo^1; p-value^2 | 2.56; 1.50; -1.06 (1.02); -; - | 2.54; 1.13; -1.42 (1.00); -0.35; 0.0002
% Superficial Cells; Baseline Mean; Week 12 Mean; Mean Change (SD); Difference from Placebo^1; p-value^2 | 1.04; 2.78; 1.75 (3.33); -; - | 1.02; 11.22; 10.20 (10.35); 8.46; <0.0001
% Parabasal Cells; Baseline Mean; Week 12 Mean; Mean Change (SD); Difference from Placebo^1; p-value^2 | 51.66; 39.68; -11.98 (29.58); -; - | 54.25; 12.74; -41.51 (36.26); -29.53; <0.0001
Vaginal pH; Baseline Mean; Week 12 Mean; Mean Change (SD); Difference from Placebo^1; p-value^2 | 6.32; 6.05; -0.27 (0.74); -; - | 6.34; 5.39; -0.94 (0.94); -0.67; <0.0001
^1Difference from placebo =INTRAROSA (Week 12 mean – Baseline mean) – Placebo (Week 12 mean – Baseline mean).
^2ANCOVA: Treatment as the main factor and Baseline value as the covariate.

16 HOW SUPPLIED/STORAGE AND HANDLING

16.1 How Supplied

INTRAROSA is supplied as white to off-white 1.3 mL solid fat bullet-shaped, smooth vaginal inserts (containing 6.5 mg of prasterone). INTRAROSA is available in small boxes of 4 blister packs containing 7 vaginal inserts (28 vaginal inserts per box). The small box (containing the vaginal inserts) is supplied inside a larger box containing 28 applicators (NDC 72495-401-28).

16.2 Storage and Handling

Store at 41°F to 86°F (5°C to 30°C). Can be stored at room temperature or in the refrigerator.

Patient Information

INTRAROSA® (in trah ROE sah)

(prasterone) vaginal inserts

What is INTRAROSA vaginal inserts?

INTRAROSA vaginal inserts are a prescription medicine used in women after menopause to treat moderate to severe pain during sexual intercourse caused by changes in and around the vagina that happen with menopause.

It is not known if INTRAROSA vaginal inserts are safe and effective in children.

Do not use INTRAROSA vaginal inserts if you have vaginal bleeding that has not been checked by your healthcare provider.

Before using INTRAROSA vaginal inserts, tell your healthcare provider about all of your medical conditions, including if you:

- have, have had, or think you may have had breast cancer. Prasterone, an ingredient in INTRAROSA vaginal inserts, is changed in your body to estrogen. Estrogen medicines are not for use in women who have, have had, or think they may have had breast cancer.
- are pregnant or plan to become pregnant. INTRAROSA is only for use in women who are past menopause. It is not known if INTRAROSA vaginal inserts will harm your unborn baby.
- are breastfeeding or plan to breastfeed. INTRAROSA vaginal inserts are only for use in women who are past menopause. It is not known if INTRAROSA passes into your breast milk.

Tell your healthcare provider about all the medicines you take, including prescription and over-the-counter medicines, vitamins, and herbal supplements.

How should I use INTRAROSA vaginal inserts?

- See the Instructions for Use at the end of this Patient Information for detailed instructions about the right way to use INTRAROSA vaginal inserts.
- Use INTRAROSA vaginal inserts exactly how your healthcare provider tells you to use it.
- Place 1 INTRAROSA vaginal insert in your vagina one time each day at bedtime, using the applicator that comes with INTRAROSA vaginal inserts.

What are the possible side effects of INTRAROSA vaginal inserts?

The most common side effects of INTRAROSA vaginal inserts are vaginal discharge and changes on Pap smear.

These are not all of the possible side effects of INTRAROSA vaginal inserts.

Call your doctor for medical advice about side effects. You may report side effects to FDA at 1-800-FDA-1088.

How should I store INTRAROSA vaginal inserts?

- Store INTRAROSA vaginal inserts between 41°F to 86°F (5°C to 30°C).
- INTRAROSA vaginal inserts can be stored at room temperature or in the refrigerator.

Keep INTRAROSA vaginal inserts and all medicines out of the reach of children.

General Information about the safe and effective use of INTRAROSA vaginal inserts.

Medicines are sometimes prescribed for purposes other than those listed in a Patient Information leaflet. Do not use INTRAROSA vaginal inserts for a condition for which it was not prescribed. Do not give INTRAROSA vaginal inserts to other people, even if they have the same symptoms that you have. It may harm them. You can ask your pharmacist or healthcare provider for information about INTRAROSA vaginal inserts that is written for health professionals.

What are the ingredients in INTRAROSA vaginal inserts?

Active ingredient: prasterone

Inactive ingredient: off-white hard fat (Witepsol)

For more information, go to www.intrarosa.com or call Millicent U.S. Inc at 1-877-810-2101.

17 PATIENT COUNSELING INFORMATION

Advise the patient to read FDA-approved patient labeling (Patient Information and Instructions for Use).

Vaginal Discharge

Inform postmenopausal women that vaginal discharge may occur with INTRAROSA [see Adverse Reactions (6.1)] .

Abnormal Pap Smear Findings

Inform postmenopausal women that abnormal Pap smear findings may occur with INTRAROSA [see Adverse Reactions (6.1)] .

Manufactured for:

Endoceutics, Inc.
Quebec City, Canada, G1V 4M7

Distributed by:

Millicent U.S. Inc.
East Hanover, NJ 07936

Instructions for Use
INTRAROSA (in trah ROE sah)
(prasterone) vaginal inserts

How should I use INTRAROSA vaginal inserts?

- INTRAROSA is a vaginal insert that you place in your vagina with an applicator that comes with INTRAROSA vaginal inserts.
- Use 1 INTRAROSA vaginal insert, one time each day at bedtime.
- Each applicator is for one time use only.
- Empty your bladder and wash your hands before handling the vaginal insert and applicator.
- Tear off 1 vaginal insert along the perforations from the 7-vaginal insert strip.

STEP 1

1a. Remove 1 applicator from the package.

1b. Pull back on the plunger until it stops to activate the applicator. The applicator must be activated before use. Place the applicator on a clean surface.

STEP 2

Slowly pull the plastic tabs on the vaginal insert away from each other while keeping the vaginal insert still between your fingers. Carefully remove the vaginal insert from the plastic wrap. If a vaginal insert falls on an unsanitary surface, replace it with a new one.

STEP 3

Place the flat end of the vaginal insert into the open end of the activated applicator as shown. You are now ready to insert the vaginal insert into your vagina.

STEP 4

Hold the applicator between your thumb and middle finger. Leave your index (pointer) finger free to press the applicator plunger after the applicator is inserted into your vagina.

STEP 5

Select the position for insertion of the vaginal insert that is most comfortable for you.

5a. Lying position

5b. Standing position

STEP 6

Gently slide the vaginal insert end of the applicator into your vagina as far as it will comfortably go.

Do not use force.

STEP 7

Press the applicator plunger with your index (pointer) finger to release the vaginal insert. Remove the applicator and throw it away after use.

For more information, go to www.intrarosa.com or call Millicent U.S. Inc at 1-877-810-2101.

This Patient Information and Instructions for Use have been approved by the U.S. Food and Drug Administration.

INTRAROSA® is a registered trademark of Endoceutics, Inc.

Manufactured for: Endoceutics, Inc., Quebec City, Canada, G1V 4M7

Distributed by: Millicent U.S. Inc., East Hanover, NJ 07936
©2020 Millicent Pharma Limited

Issued: June 2020